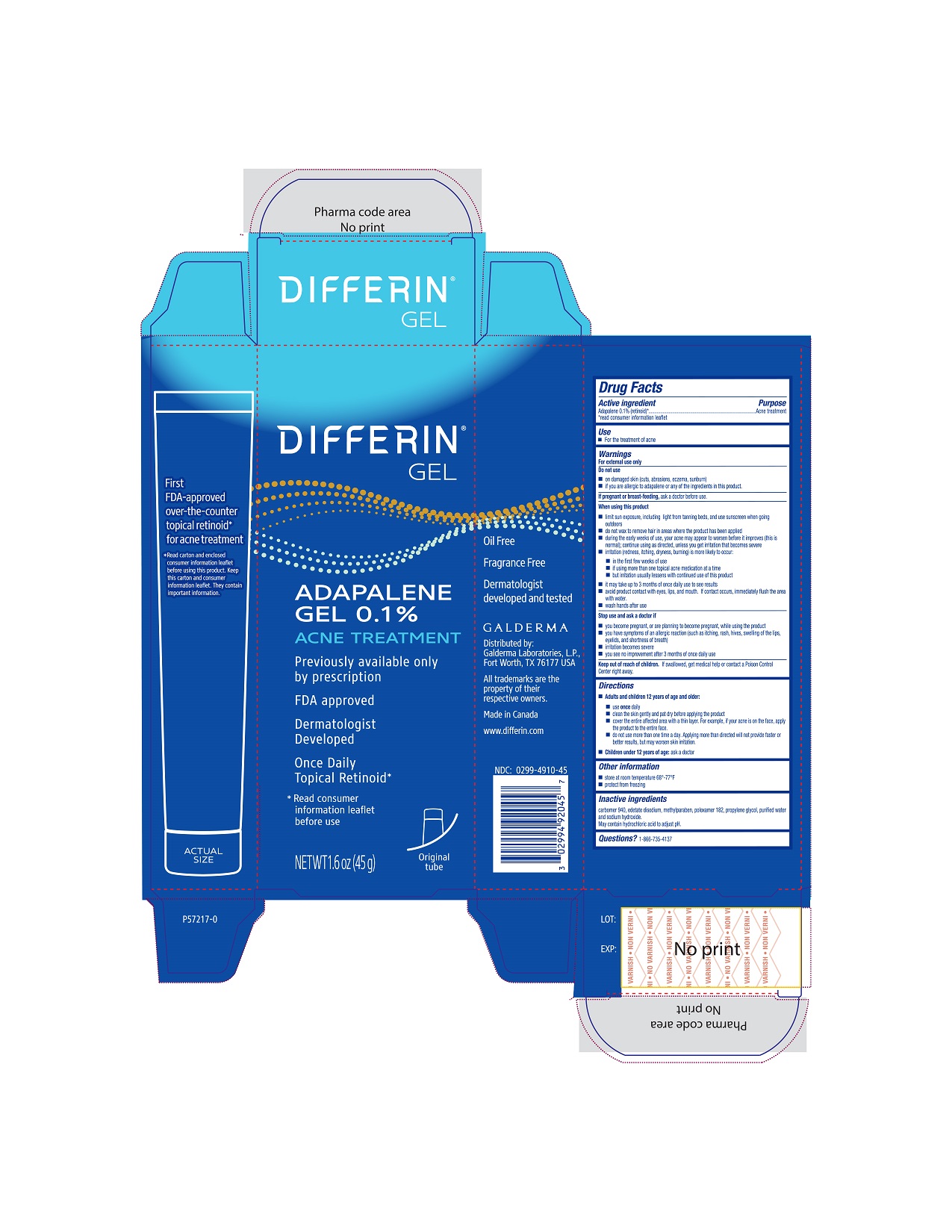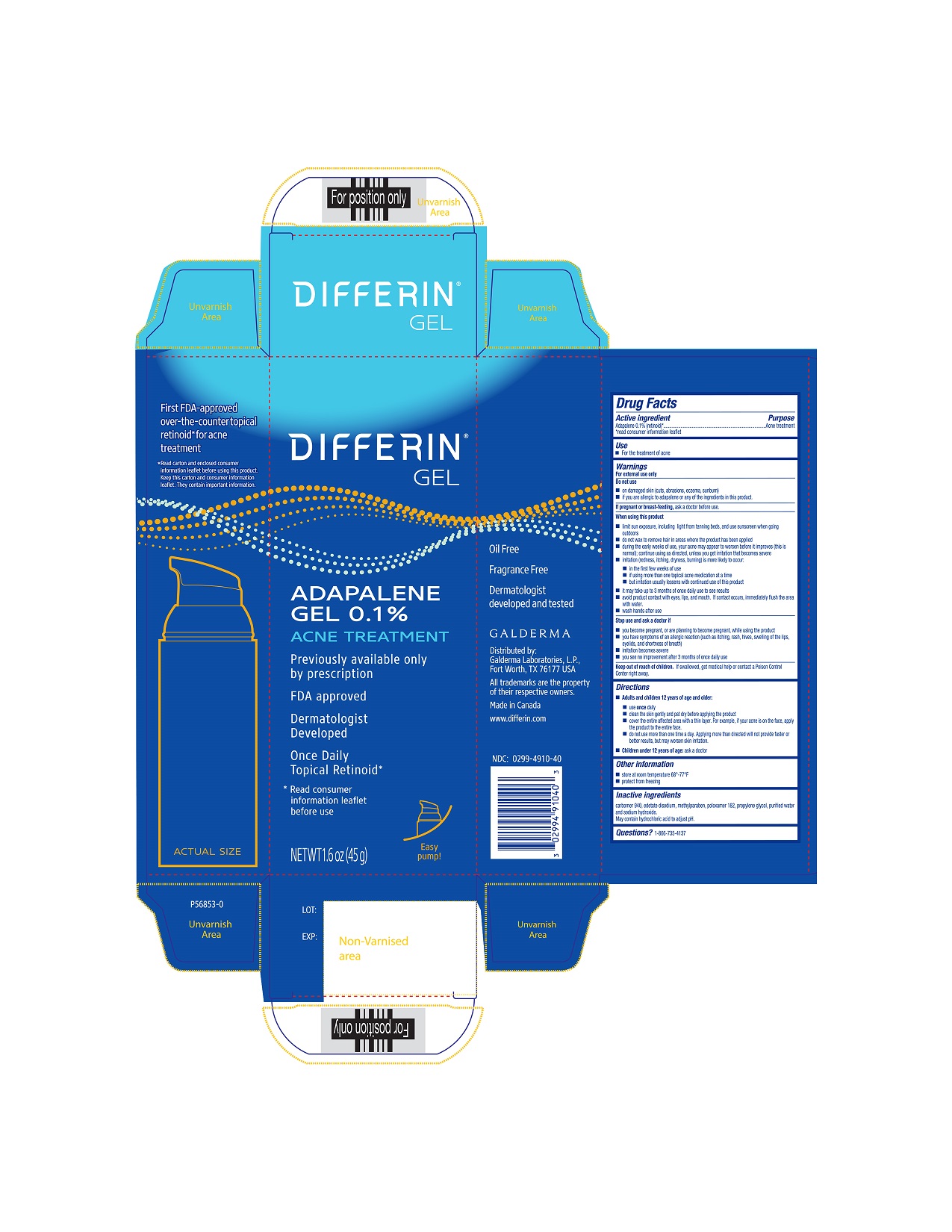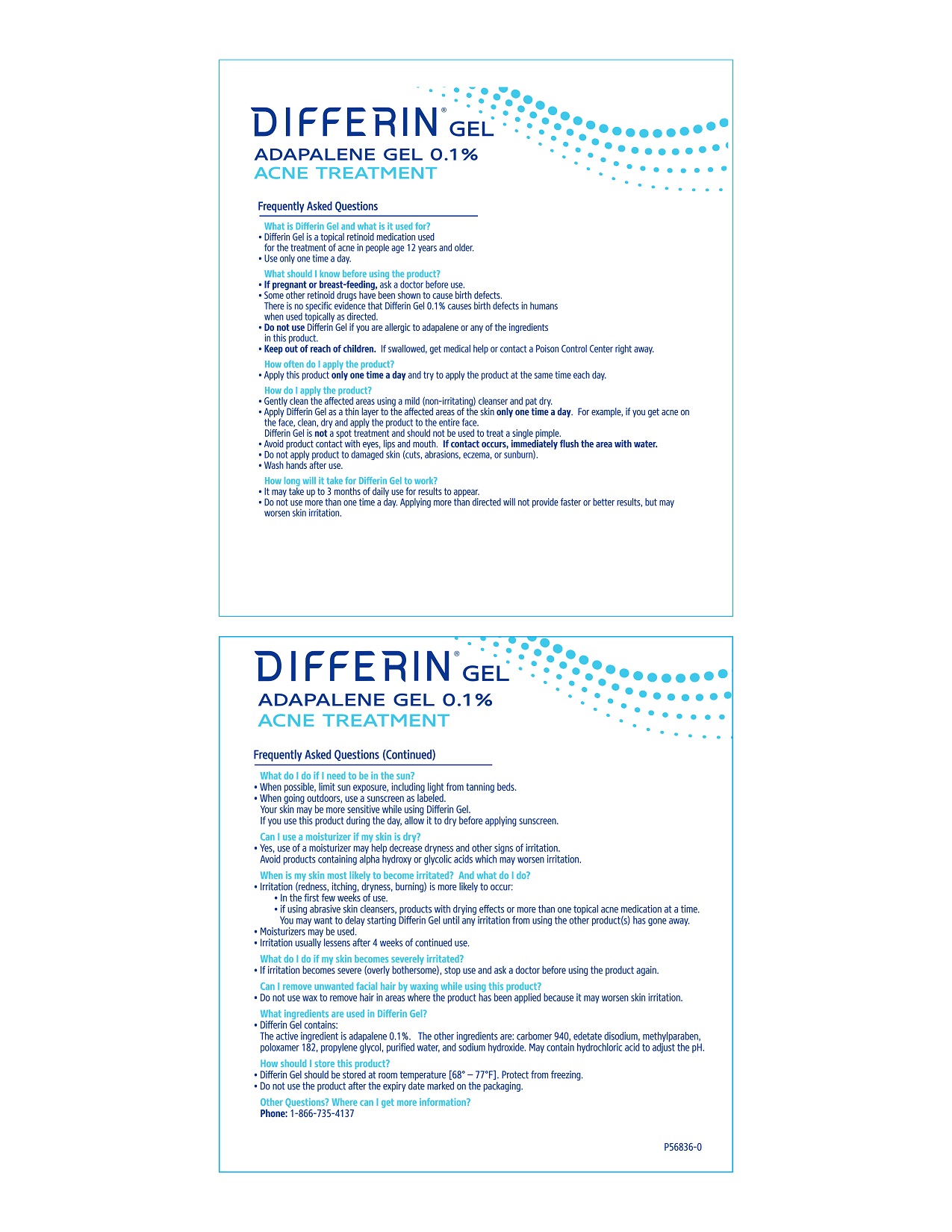 DRUG LABEL: Differin 
NDC: 0299-4910 | Form: GEL
Manufacturer: Galderma Laboratories, L.P.
Category: otc | Type: HUMAN OTC DRUG LABEL
Date: 20221207

ACTIVE INGREDIENTS: ADAPALENE 1 mg/1 g
INACTIVE INGREDIENTS: CARBOMER HOMOPOLYMER TYPE C (ALLYL PENTAERYTHRITOL CROSSLINKED); EDETATE DISODIUM; METHYLPARABEN; POLOXAMER 182; PROPYLENE GLYCOL; WATER; SODIUM HYDROXIDE; HYDROCHLORIC ACID

DIFFERIN® GEL
ADAPALENE GEL, 0.1%

Drug Facts

Active ingredient
Adapalene 0.1% (retinoid)*
*read consumer information leaflet

Purpose

acne treatment

Use

- For the treatment of acne

Warnings

For external use only

Do not use

- on damaged skin (cuts, abrasions, eczema, sunburn)
- if you are allergic to adapalene or any of the ingredients in this product.

If pregnant or breast-feeding, ask a doctor before use.

When using this product

- limit sun exposure, including light from tanning beds, and use sunscreen when going outdoors
- do not wax to remove hair in areas where the product has been applied
- during the early weeks of use, your acne may appear to worsen before it improves (this is normal); continue using as directed, unless you get irritation that becomes severe
- irritation (redness, itching, dryness, burning) is more likely to occur:
  - in the first few weeks of use
  - if using more than one topical acne medication at a time
  - but irritation usually lessens with continued use of this product
- it may take up to 3 months of once daily use to see results
- avoid product contact with eyes, lips, and mouth. If contact occurs, immediately flush the area with water.
- wash hands after use

Stop use and ask doctor if

- you become pregnant, or are planning to become pregnant, while using the product
- you have symptoms of an allergic reaction (such as itching, rash, hives, swelling of the lips, eyelids, and shortness of breath)
- irritation becomes severe
- you see no improvement after 3 months of once daily use

Keep out of reach of children.

If swallowed, get medical help or contact a Poison Control Center right away.

Directions Adults and children 12 years of age and older:

- use once daily
- clean the skin gently and pat dry before applying the product
- cover the entire affected area with a thin layer. For example, if your acne is on the face, apply the product to the entire face.
- do not use more than one time a day. Applying more than directed will not provide faster or better results, but may worsen skin irritation.

Children under 12 years of age: ask a doctor

Other information

- store at room temperature 68°-77°F
- protect from freezing

Inactive Ingredients

carbomer 940, edetate disodium, methylparaben, poloxamer 182,
propylene glycol, purified water and sodium hydroxide.
May contain hydrochloric acid to adjust pH.

Patient Leaflet

DIFFERIN GEL
ADAPALENE GEL 0.1%
ACNE TREATMENT

Frequently Asked Questions

What is Differin Gel and what is it used for?

• Differin Gel is a topical retinoid medication used for the treatment of acne in people 12 years and older.
• Use only one time a day.

What should I know before using the product?

• If pregnant or breast-feeding, ask a doctor before use.
• Some other retinoid drugs have been shown to cause birth defects. There is no specific evidence that Differin Gel 0.1% causes birth defects in humans when used topically as directed.
• Do not use Differin Gel if you are allergic to adapalene or any of the ingredients in this product.
• Keep out of reach of children. If swallowed, get medical help or contact a Poison Control Center right away.

How often do I apply the product?

• Apply this product only one time a day and try to apply the product at the same time each day.

How do I apply the product?

• Gently clean the affected areas using a mild (non-irritating) cleanser and pat dry.
• Apply Differin Gel as a thin layer to the affected areas of the skin onlyone time a day. For example, if you get acne on the face, clean, dry and apply the product to the entire face. Differin Gel is not a spot treatment and should not be used to treat a single pimple.
• Avoid product contact with eyes, lips and mouth. If contact occurs, immediately flush the area with water.
• Do not apply product to damaged skin (cuts, abrasions, eczema, or sunburn).
• Wash hands after use.

How long will it take for Differin Gel to work?
• It may take up to 3 months of daily use for results to appear.
• Do not use more than one time a day. Applying more than directed will not provide faster or better results, but may worsen skin irritation.

DIFFERIN GEL
ADAPALENE GEL 0.1%
ACNE TREATMENT
Frequently Asked Questions (Continued)

What do I do if I need to be in the sun?

• When possible, limit sun exposure, including light from tanning beds.

• When going outdoors, use a sunscreen as labeled. Your skin may be more sensitive when using Differin Gel. If you use this product during the day, allow it to dry before applying sunscreen.

Can I use a moisturizer if my skin is dry?
•Yes, use of a moisturizer may help decrease dryness and other signs of irritation. Avoid products containing alpha hydroxyl or glycolic acids which may worsen irritation.

When is my skin most likely to become irritated? And what do I do?

• Irritation (redness, itching, dryness, burning) is more likely to occur:
• In the first weeks of use.
• If using abrasive skin cleansers, products with drying effects or more than one topical acne medication at a time. You may want to delay starting Differin Gel until any irritation from using the other product(s) has gone away.
• Moisturizers may be used.
• Irritation usually lessens after 4 weeks of continued use.

What do I do if my skin becomes severely irritated?

• If irritation becomes severe (overly bothersome), stop use and ask a doctor before using the product again.

Can I remove unwanted facial hair by waxing while using this product?
• Do not use wax to remove hair in areas where the product has been applied because it may worsen skin irritation.

What ingredients are used in Differin?

• Differin Gel contains:
The active ingredient is adapalene 0.1%. The other ingredients are: carbomer 940, edetate disodium, methylparaben, poloxamer 182, propylene glycol, purified water, and sodium hydroxide. May contain hydrochloric acid to adjust pH.

How should I store this product?

• Differin Gel should be stored at room temperature [68° - 77°]. Protect from freezing.
• Do not use the product after the expiry date marked on the packaging.

Other Questions? Where can I get information?
Phone: 1-866-735-4137

P56836-0

PRINCIPAL DISPLAY PANEL - 45g Carton (Tube)

DIFFERIN® GEL

ADAPALENE GEL 0.1%
ACNE TREATMENT

Previously available only by prescription

FDA approved

Dermatologist Developed

Once Daily Topical Retinoid*

* Read consumer information leaflet before use

NET WT 1.6 OZ (45 g)

Distributed by:
Galderma Laboratories, L.P.
Fort Worth, TX 76177 USA

All trademarks are the property of their respective owners.
Made in Canada

P57217-0

PRINCIPAL DISPLAY PANEL - 45g Carton (Pump)

DIFFERIN® GEL

ADAPALENE GEL 0.1%
ACNE TREATMENT

Previously available only by prescription

FDA approved

Dermatologist Developed

Once Daily Topical Retinoid*

* Read consumer information leaflet before use

Easy pump!

NET WT 1.6 OZ (45 g)

Distributed by:
Galderma Laboratories, L.P.
Fort Worth, TX 76177 USA

All trademarks are the property of their respective owners.
Made in Canada
www.differin.com

P56853-0